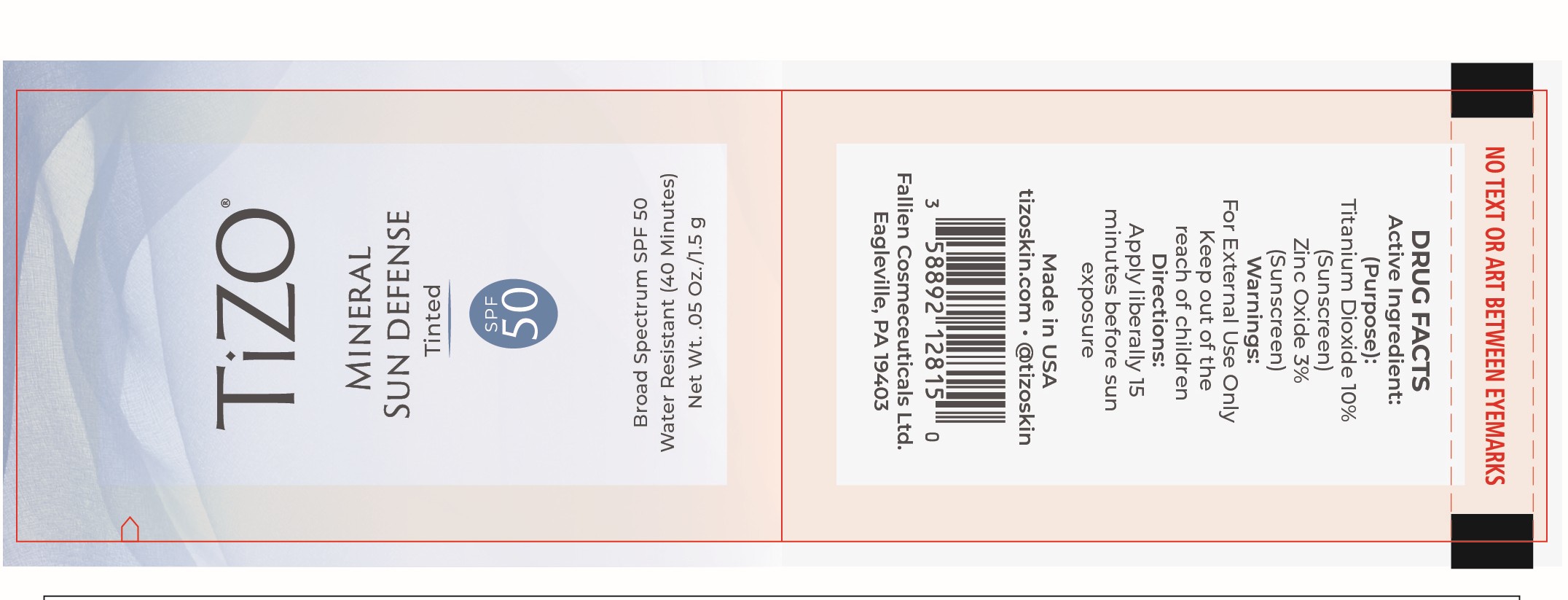 DRUG LABEL: TiZO Mineral Sun Defense SPF 50
NDC: 58892-128 | Form: CREAM
Manufacturer: Fallien Cosmeceuticals Ltd.
Category: otc | Type: HUMAN OTC DRUG LABEL
Date: 20250128

ACTIVE INGREDIENTS: ZINC OXIDE 30 mg/1 g; TITANIUM DIOXIDE 100 mg/1 g
INACTIVE INGREDIENTS: TETRAHEXYLDECYL ASCORBATE; TRIETHOXYCAPRYLYLSILANE; CAPRYLIC/CAPRIC TRIGLYCERIDE; GLYCERIN; BISMUTH OXYCHLORIDE; CAPRYLHYDROXAMIC ACID; ISOHEXADECANE; ISODODECANE; CAPRYLYL GLYCOL; CETEARETH-20; ETHYLHEXYL HYDROXYSTEARATE BENZOATE; IRON OXIDES; MICA; MICROCRYSTALLINE WAX; EDETATE DISODIUM ANHYDROUS; TOCOPHEROL; OCTYLDODECYL NEOPENTANOATE; PEG-30 DIPOLYHYDROXYSTEARATE; ALPHA-TOCOPHEROL ACETATE; SODIUM CHLORIDE; TRIETHANOLAMINE; MELISSA OFFICINALIS WHOLE; CYCLOHEXASILOXANE; CYCLOPENTASILOXANE; DIMETHICONE; WATER

Active Ingredients:

Titanium Dioxide 10% Zinc Oxide 3%

(Purpose)

Sunscreen

Directions:

Apply liberally 15 minutes before sun exposure.

Warning and Directions:

For external use only. Apply liberally 15 minutes before sun exposure.

Warning:

For external use only.

INACTIVE INGREDIENT

Bismuth Oxychloride, Capric/Caprylic Triglyceride, Caprylhydroxamic Acid, Caprylyl Glycol, Ceteareth-20, Cyclohexasiloxane, Cyclopentasiloxane, Dimethicone, Disodium EDTA, Ethylhexyl Hydroxystearate Benzoate, Glycerin, Iron Oxides, Isododecane, Isohexadecane, Melissa Officinalis (Balm Mint) Extract, Mica, Microcrystalline Wax, Octyldodecyl Neopentanoate, PEG-30 Dipolyhydroxystearate, Sodium Chloride, Tetrahexyldecyl Ascorbate, Tocopheryl Acetate, Tocopherol, Triethanolamine, Triethoxycaprylylsilane, Water